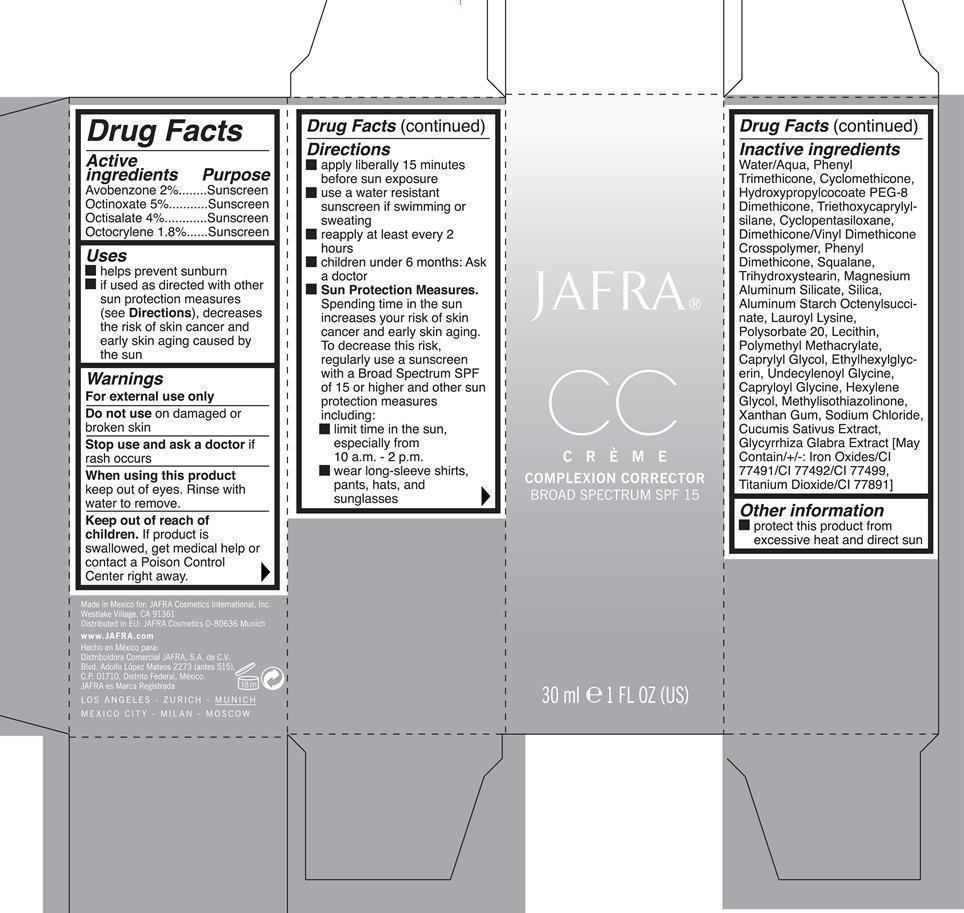 DRUG LABEL: CC Cream Complexion Corrector Dark Broad Spectrum SPF 15
NDC: 68828-193 | Form: CREAM
Manufacturer: Jafra cosmetics International
Category: otc | Type: HUMAN OTC DRUG LABEL
Date: 20200623

ACTIVE INGREDIENTS: AVOBENZONE 2 g/100 mL; OCTINOXATE 5 g/100 mL; OCTISALATE 4 g/100 mL; OCTOCRYLENE 1.8 g/100 mL
INACTIVE INGREDIENTS: WATER; PHENYL TRIMETHICONE; CYCLOMETHICONE; HYDROXYPROPYLCOCOATE PEG-8 DIMETHICONE; TRIETHOXYCAPRYLYLSILANE; CYCLOMETHICONE 5; DIMETHICONE/VINYL DIMETHICONE CROSSPOLYMER (SOFT PARTICLE); SQUALANE; TRIHYDROXYSTEARIN; MAGNESIUM ALUMINUM SILICATE; SILICON DIOXIDE; ALUMINUM STARCH OCTENYLSUCCINATE; LAUROYL LYSINE; POLYSORBATE 20; LECITHIN, SOYBEAN; POLY(METHYL METHACRYLATE; 450000 MW); CAPRYLYL GLYCOL; ETHYLHEXYLGLYCERIN; UNDECYLENOYL GLYCINE; CAPRYLOYL GLYCINE; HEXYLENE GLYCOL; METHYLISOTHIAZOLINONE; XANTHAN GUM; SODIUM CHLORIDE; CUCUMBER; GLYCYRRHIZA GLABRA; FERRIC OXIDE RED; FERRIC OXIDE YELLOW; FERROSOFERRIC OXIDE; TITANIUM DIOXIDE

Jafra CC Creme Complexion Corrector Broad Spectrum SPF 15

Active Ingredients Purpose

Avobenzone 2% Sunscreen

Octinoxate 5% Sunscreen

Octisalate 4% Sunscreen

Octocrylene 1.8% Sunscreen

Uses

helps prevent sunburn

if used as directed with other sun protection measures (see Directions), decreases the risk of skin cancer and early skin aging caused by the sun

Keep out of reach of children

Stop use and ask a doctor if rash occurs

WARNINGS

For External use only

Do not use on damaged or broken skin

When using this product, keep out of eyes. Rinse with water to remove.

If product is swallowed, get medical help or contact a Poison Control Center right away.

Directions

apply liberally 15 minutes before sun exposure

use a water resistant sunscreen if swimming or sweating

reapply at least every 2 hours

children under 6 months

Sun Protection Measures

Spending time in the sun increases your risk of skin cancer and early skin aging. To decrease this risk of 15 or higher and other sun protection measures including:

- limit time in the sun, especially from 10 a.m. - 2p.m.

- wear long sleeve-shirts, pants, hats, and sunglasses

INACTIVE INGREDIENT

Water/Aqua, Phenyl Trimethicone, Cyclomethicone, Hydroxypropylcocoate PEG-8 Dimethicone, Triethoxycaprylylsilane, Cyclopentasiloxane, Dimethicone/Vinyl Dimethicone Crosspolymer, Phenyl Dimethicone, Squalane, Trihydroxystearin, Magnesium Aluminum Silicate, Silica, aluminum Starch Octenylsuccinate, Lauryl Lysine, Polysorbate 20, Lecithin, Polymethyl Methacrylate, Caprylyl Glycol, Ethylhexylglycerin, Undecylenoyl Glycine, Hexylene Glycol, Methylisothiazolinone, Xanthan Gum, Sodium Chloride, Cucumis Sativus Extract , Glycyrrhiza Glabra Extract [May contain/+/-: Iron Oxides/CI 77491/CI 77492/77499, Titanium Dioxide/CI 77891]

PACKAGE LABEL

Jafra CC Creme Complexion Corrector

Complexion Corrector Broad Spectrum SPF 15

30 ml 1 Fl Oz (US)